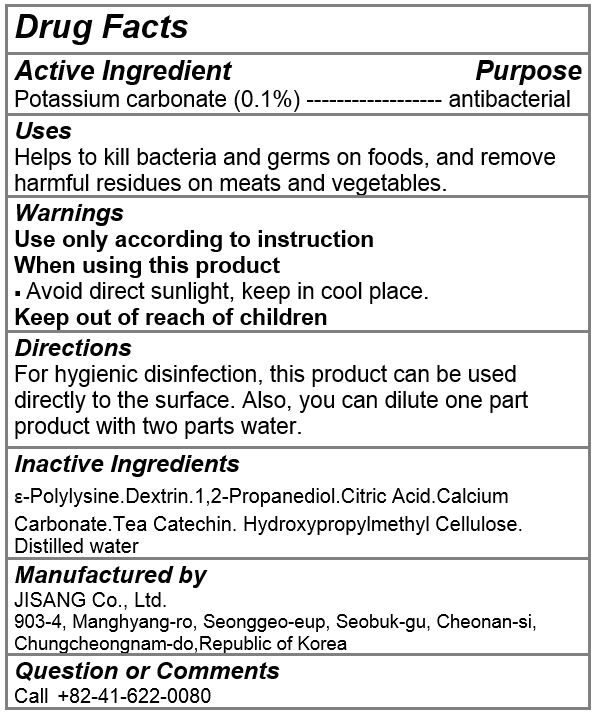 DRUG LABEL: ZEROQ  FOOD
NDC: 80643-0004 | Form: LIQUID
Manufacturer: JISANG Co., Ltd.
Category: otc | Type: HUMAN OTC DRUG LABEL
Date: 20200928

ACTIVE INGREDIENTS: POTASSIUM CARBONATE 0.5 g/500 mL
INACTIVE INGREDIENTS: PROPYLENE GLYCOL; CITRIC ACID MONOHYDRATE; HYPROMELLOSE, UNSPECIFIED; WATER

ACTIVE INGREDIENT

potassium carbonate

INACTIVE INGREDIENT

e-polylysine, dextrin, 1,2-propanediol, citric acid, tea catechin, hydroxypropylmethyl cellulose, water

PURPOSE

Helps to kill bacteria and germs on foods, and remove harmful residues on meats and vegetables.

keep out of reach of the children

INDICATIONS AND USAGE

For hygienic disinfection, this product can be used directly to the surface. Also, you can dilute one part product with two parts water.

WARNINGS

Use only according to instruction

When using this product

Avoid direct sunlight, keep in cool place.

Keep out of reach of children

DOSAGE AND ADMINISTRATION

for external use only